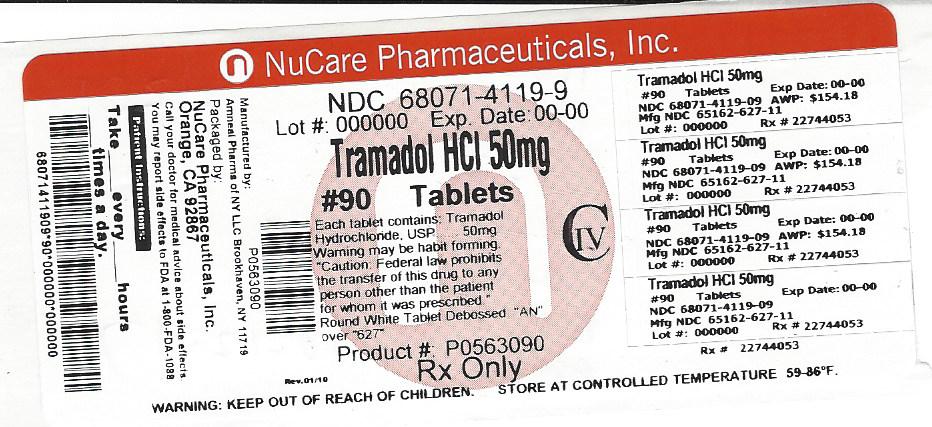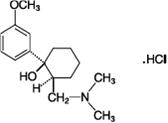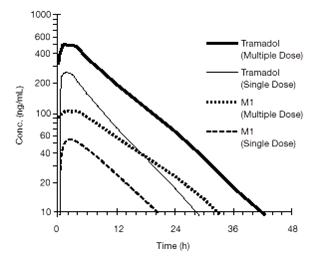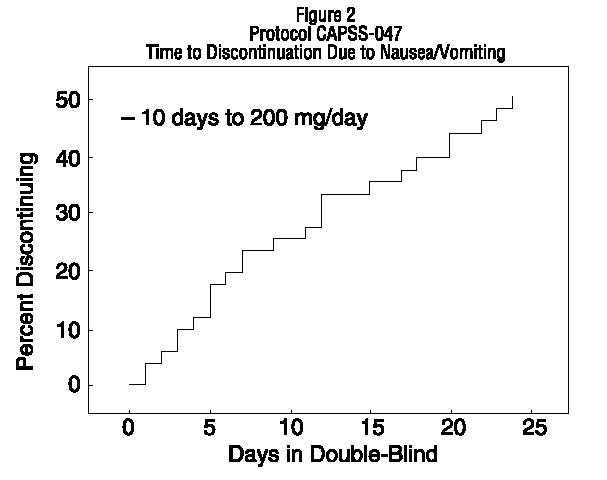 DRUG LABEL: Tramadol Hydrochloride
NDC: 68071-4119 | Form: TABLET, COATED
Manufacturer: NuCare Pharmaceuticals,Inc.
Category: prescription | Type: HUMAN PRESCRIPTION DRUG LABEL
Date: 20250203
DEA Schedule: CIV

ACTIVE INGREDIENTS: TRAMADOL HYDROCHLORIDE 50 mg/1 1
INACTIVE INGREDIENTS: LACTOSE MONOHYDRATE; SODIUM STARCH GLYCOLATE TYPE A POTATO; MAGNESIUM STEARATE; CELLULOSE, MICROCRYSTALLINE; POLYETHYLENE GLYCOL, UNSPECIFIED; POLYSORBATE 80; TITANIUM DIOXIDE; HYPROMELLOSES; STARCH, CORN

Tramadol Hydrochloride Tablets, USP CIV

WARNING: ADDICTION, ABUSE, AND MISUSE; LIFETHREATENING RESPIRATORY DEPRESSION; ACCIDENTAL INGESTION; NEONATAL OPIOID WITHDRAWAL SYNDROME; INTERACTIONS WITH DRUGS AFFECTING CYTOCHROME P450 ISOENZYMES; and RISKS FROM CONCOMITANT USE WITH BENZODIAZEPINES OR OTHER CNS DEPRESSANTS

ADDICTION, ABUSE AND MISUSE

Tramadol HCl exposes patients and other users to the risks of opioid addiction, abuse and misuse, which can lead to overdose and death. Assess each patient’s risk prior to prescribing tramadol HCl, and monitor all patients regularly for the development of these behaviors and conditions (see WARNINGS).

LIFE-THREATENING RESPIRATORY DEPRESSION

Serious, life-threatening, or fatal respiratory depression may occur with use of tramadol HCl. Monitor for respiratory depression, especially during initiation of tramadol HCl or following a dose increase (see WARNINGS).

ACCIDENTAL INGESTION

Accidental ingestion of tramadol HCl, especially by children, can be fatal (see WARNINGS).

NEONATAL OPIOID WITHDRAWAL SYNDROME

Prolonged use of tramadol HCl during pregnancy can result in neonatal opioid withdrawal syndrome, which may be life-threatening if not recognized and treated, and requires management according to protocols developed by neonatology experts. If opioid use is required for a prolonged period in a pregnant woman, advise the patient of the risk of neonatal opioid withdrawal syndrome and ensure that appropriate treatment will be available (see WARNINGS).

INTERACTIONS WITH DRUGS AFFECTING CYTOCHROME P450 ISOENZYMES

The effects of concomitant use or discontinuation of cytochrome P450 3A4 inducers, 3A4 inhibitors, or 2D6 inhibitors with tramadol are complex. Use of cytochrome P450 3A4 inducers, 3A4 inhibitors, or 2D6 inhibitors with

Tramadol HCl requires careful consideration of the effects on the parent drug, tramadol, and the active metabolite, M1 (see WARNINGS, PRECAUTIONS; Drug Interactions).

RISKS FROM CONCOMITANT USE WITH BENZODIAZEPINES OR OTHER CNS DEPRESSANTS

Concomitant use of opioids with benzodiazepines or other central nervous system (CNS) depressants, including alcohol, may result in profound sedation, respiratory depression, coma, and death (see WARNINGS, PRECAUTIONS; Drug Interactions).

- Reserve concomitant prescribing of tramadol HCl and benzodiazepines or other CNS depressants for use in patients for whom alternative treatment options are inadequate.
- Limit treatment to the minimum effective dosages and durations.
- Follow patients for signs and symptoms of respiratory depression and sedation.

DESCRIPTION

Tramadol hydrochloride (HCl) tablets, USP are an opioid agonist. The chemical name for tramadol HCl, USP is (±) cis-2-[(dimethylamino)methyl]-1-(3-methoxyphenyl) cyclohexanol hydrochloride. The structural formula is:

The molecular weight of tramadol HCl, USP is 299.8. Tramadol HCl, USP is a white, bitter, crystalline and odorless powder. It is readily soluble in water and ethanol and has a pKa of 9.41. The n-octanol/water log partition coefficient (logP) is 1.35 at pH 7. Tramadol HCl tablets, USP contain 50 mg of tramadol HCl, USP and are white in color.

Inactive ingredients in the tablet are hypromellose, lactose monohydrate, magnesium stearate, microcrystalline cellulose, polyethylene glycol, polysorbate 80, pregelatinized starch, sodium starch glycolate, and titanium dioxide.

CLINICAL PHARMACOLOGY

Mechanism of Action

Tramadol HCl contains tramadol, an opioid agonist and inhibitor of norepinephrine and serotonin re-uptake. Although the mode of action is not completely understood, the analgesic effect of tramadol is believed to be due to both binding to µ-opioid receptors and weak inhibition of re-uptake of norepinephrine and serotonin.

Opioid activity is due to both low affinity binding of the parent compound and higher affinity binding of the O-demethylated metabolite M1 to µ-opioid receptors. In animal models, M1 is up to 6 times more potent than tramadol in producing analgesia and 200 times more potent in µ-opioid binding. Tramadol-induced analgesia is only partially antagonized by the opiate antagonist naloxone in several animal tests. The relative contribution of both tramadol and M1 to human analgesia is dependent upon the plasma concentrations of each compound (see CLINICAL PHARMACOLOGY; Pharmacokinetics).

Tramadol has been shown to inhibit reuptake of norepinephrine and serotonin in vitro, as have some other opioid analgesics. These mechanisms may contribute independently to the overall analgesic profile of tramadol. Analgesia in humans begins approximately within one hour after administration and reaches a peak in approximately two to three hours.

Pharmacodynamics

Effects on the Central Nervous System

Tramadol produces respiratory depression by direct action on brain stem respiratory centers. The respiratory depression involves a reduction in the responsiveness of the brain stem respiratory centers to both increases in carbon dioxide tension and electrical stimulation.

Tramadol causes miosis, even in total darkness. Pinpoint pupils are a sign of opioid overdose but are not pathognomonic (e.g., pontine lesions of hemorrhagic or ischemic origins may produce similar findings). Marked mydriasis rather than miosis may be seen due to hypoxia in overdose situations.

Effects on the Gastrointestinal Tract and Other Smooth Muscle

Tramadol causes a reduction in motility associated with an increase in smooth muscle tone in the antrum of the stomach and duodenum. Digestion of food in the small intestine is delayed and propulsive contractions are decreased. Propulsive peristaltic waves in the colon are decreased, while tone may be increased to the point of spasm resulting in constipation. Other opioid-induced effects may include a reduction in biliary and pancreatic secretions, spasm of sphincter of Oddi, and transient elevations in serum amylase.

Effects on the Cardiovascular System

Tramadol produces peripheral vasodilation, which may result in orthostatic hypotension or syncope. Manifestations of peripheral vasodilation may include pruritus, flushing, red eyes, sweating and/or orthostatic hypotension.

Effects on the Endocrine System

Opioids inhibit the secretion of adrenocorticotropic hormone (ACTH), cortisol, and luteinizing hormone (LH) in humans. They also stimulate prolactin, growth hormone (GH) secretion, and pancreatic secretion of insulin and glucagon (see WARNINGS; ADVERSE REACTIONS).

Chronic use of opioids may influence the hypothalamic-pituitary-gonadal axis, leading to androgen deficiency that may manifest as low libido, impotence, erectile dysfunction, amenorrhea, or infertility. The causal role of opioids in the clinical syndrome of hypogonadism is unknown because the various medical, physical, lifestyle, and psychological stressors that may influence gonadal hormone levels have not been adequately controlled for in studies conducted to date (see ADVERSE REACTIONS).

Effects on the Immune System

Opioids have been shown to have a variety of effects on components of the immune system in in vitro and animal models. The clinical significance of these findings is unknown. Overall, the effects of opioids appear to be modestly immunosuppressive.

Concentration–Efficacy Relationships

The minimum effective analgesic concentration will vary widely among patients, especially among patients who have been previously treated with potent opioid agonists. The minimum effective analgesic concentration of tramadol for any individual patient may increase over time due to an increase in pain, the development of a new pain syndrome and/or the development of analgesic tolerance (see DOSAGE AND ADMINISTRATION).

Concentration–Adverse Reaction Relationships

There is a relationship between increasing tramadol plasma concentration and increasing frequency of dose-related opioid adverse reactions such as nausea, vomiting, CNS effects, and respiratory depression. In opioid-tolerant patients, the situation may be altered by the development of tolerance to opioid-related adverse reactions (see DOSAGE AND ADMINISTRATION).

Pharmacokinetics

The analgesic activity of tramadol HCl is due to both parent drug and the M1 metabolite (see CLINICAL PHARMACOLOGY; Pharmacodynamics). Tramadol is administered as a racemate and both the [-] and [+] forms of both tramadol and M1 are detected in the circulation. Linear pharmacokinetics have been observed following multiple doses of 50 and 100 mg to steady-state.

Absorption

The mean absolute bioavailability of a 100 mg oral dose is approximately 75%. The mean peak plasma concentration of racemic tramadol and M1 occurs at two and three hours, respectively, after administration in healthy adults. In general, both enantiomers of tramadol and M1 follow a parallel time course in the body following single and multiple doses although small differences (~ 10%) exist in the absolute amount of each enantiomer present.

Steady-state plasma concentrations of both tramadol and M1 are achieved within two days with four times per day dosing. There is no evidence of self-induction (see Figure 1 and Table 1 below).

Figure 1: Mean Tramadol and M1 Plasma Concentration Profiles after a Single 100 mg Oral Dose and after Twenty-Nine 100 mg Oral Doses of Tramadol HCl given four times per day.

Table 1 Mean (%CV) Pharmacokinetic Parameters for Racemic Tramadol and M1 Metabolite

Population/ Dosage Regimena | Parent Drug/ Metabolite | Peak Conc. (ng/mL) | Time to Peak (hrs) | Clearance/Fb; (mL/min/Kg) | t1/2 (hrs)
Healthy Adults,; 100 mg qid, MD p.o. | Tramadol; M1 | 592 (30); 110 (29) | 2.3 (61); 2.4 (46) | 5.90 (25)c | 6.7 (15); 7.0 (14)
Healthy Adults,; 100 mg SD p.o. | Tramadol; M1 | 308 (25); 55.0 (36) | 1.6 (63); 3.0 (51) | 8.50 (31)c | 5.6 (20); 6.7 (16)
Geriatric, (>75 yrs); 50 mg SD p.o. | Tramadol; M1 | 208 (31)d | 2.1 (19)d | 6.89 (25)c | 7.0 (23)d
Hepatic Impaired,; 50 mg SD p.o. | Tramadol; M1 | 217 (11); 19.4 (12) | 1.9 (16); 9.8 (20) | 4.23 (56)c | 13.3 (11); 18.5 (15)
Renal Impaired,; CLcr10 to 30 mL/min; 100 mg SD i.v. | Tramadol; M1 | c; c | c; c | 4.23 (54)c | 10.6 (31); 11.5 (40)
Renal Impaired,; CLcr<5 mL/min; 100 mg SD i.v. | Tramadol; M1 | c; c | c; c | 3.73 (17)c | 11.0 (29); 16.9 (18)

a SD = Single dose, MD = Multiple dose, p.o.= Oral administration, i.v.= Intravenous administration, q.i.d. = Four times daily

b F represents the oral bioavailability of tramadol

c Not applicable

d Not measured

Food Effects

Oral administration of tramadol HCl with food does not significantly affect its rate or extent of absorption, therefore, tramadol HCl can be administered without regard to food.

Distribution

The volume of distribution of tramadol was 2.6 and 2.9 liters/kg in male and female subjects, respectively, following a 100 mg intravenous dose. The binding of tramadol to human plasma proteins is approximately 20% and binding also appears to be independent of concentration up to 10 mcg/mL. Saturation of plasma protein binding occurs only at concentrations outside the clinically relevant range.

Elimination

Tramadol is eliminated primarily through metabolism by the liver and the metabolites are eliminated primarily by the kidneys. The mean (%CV) apparent total clearance of tramadol after a single 100 mg oral dose is 8.50 (31) mL/min/kg. The mean terminal plasma elimination half-lives of racemic tramadol and racemic M1 are 6.3 ± 1.4 and 7.4 ± 1.4 hours, respectively. The plasma elimination half-life of racemic tramadol increased from approximately six hours to seven hours upon multiple dosing.

Metabolism

Tramadol is extensively metabolized after oral administration by a number of pathways, including CYP2D6 and CYP3A4, as well as by conjugation of parent and metabolites. Approximately 30% of the dose is excreted in the urine as unchanged drug, whereas 60% of the dose is excreted as metabolites. The remainder is excreted either as unidentified or as unextractable metabolites. The major metabolic pathways appear to be N- and O-demethylation and glucuronidation or sulfation in the liver. One metabolite (O-desmethyltramadol, denoted M1) is pharmacologically active in animal models. Formation of M1 is dependent on CYP2D6 and as such is subject to inhibition, which may affect the therapeutic response (see PRECAUTIONS; Drug Interactions).

Approximately 7% of the population has reduced activity of the CYP2D6 isoenzyme of cytochrome P-450. These individuals are “poor metabolizers” of debrisoquine, dextromethorphan, tricyclic antidepressants, among other drugs. Based on a population PK analysis of Phase I studies in healthy subjects, concentrations of tramadol were approximately 20% higher in “poor metabolizers” versus “extensive metabolizers”, while M1 concentrations were 40% lower. Concomitant therapy with inhibitors of CYP2D6 such as fluoxetine, paroxetine and quinidine could result in significant drug interactions. In vitro drug interaction studies in human liver microsomes indicate that inhibitors of CYP2D6 such as fluoxetine and its metabolite norfluoxetine, amitriptyline and quinidine inhibit the metabolism of tramadol to various degrees, suggesting that concomitant administration of these compounds could result in increases in tramadol concentrations and decreased concentrations of M1. The full pharmacological impact of these alterations in terms of either efficacy or safety is unknown. Concomitant use of SEROTONIN re-uptake INHIBITORS and MAO INHIBITORS may enhance the risk of adverse events, including seizure and serotonin syndrome (see WARNINGS).

Excretion

Tramadol metabolites are eliminated primarily by the kidneys.

Special Populations

Hepatic Impairment

Metabolism of tramadol and M1 is reduced in patients with advanced cirrhosis of the liver, resulting in both a larger area under the concentration time curve for tramadol and longer tramadol and M1 elimination half-lives (13 hrs. for tramadol and 19 hrs. for M1). In cirrhotic patients, adjustment of the dosing regimen is recommended (see DOSAGE AND ADMINISTRATION).

Renal Impairment

Impaired renal function results in a decreased rate and extent of excretion of tramadol and its active metabolite, M1. In patients with creatinine clearances of less than 30 mL/min, adjustment of the dosing regimen is recommended (see DOSAGE AND ADMINISTRATION). The total amount of tramadol and M1 removed during a 4-hour dialysis period is less than 7% of the administered dose.

Age: Geriatric

Healthy elderly subjects aged 65 to 75 years have plasma tramadol concentrations and elimination half-lives comparable to those observed in healthy subjects less than 65 years of age. In subjects over 75 years, maximum serum concentrations are elevated (208 vs. 162 ng/mL) and the elimination half-life is prolonged (7 vs. 6 hours) compared to subjects 65 to 75 years of age. Adjustment of the daily dose is recommended for patients older than 75 years (see DOSAGE AND ADMINISTRATION).

Sex

The absolute bioavailability of tramadol was 73% in males and 79% in females. The plasma clearance was 6.4 mL/min/kg in males and 5.7 mL/min/kg in females following a 100 mg IV dose of tramadol. Following a single oral dose, and after adjusting for body weight, females had a 12% higher peak tramadol concentration and a 35% higher area under the concentration-time curve compared to males. The clinical significance of this difference is unknown.

Poor / Extensive Metabolizers, CYP2D6

The formation of the active metabolite, M1, is mediated by CYP2D6, a polymorphic enzyme. Approximately 7% of the population has reduced activity of the CYP2D6 isoenzyme of cytochrome P450 metabolizing enzyme system. These individuals are “poor metabolizers” of debrisoquine, dextromethorphan and tricyclic antidepressants, among other drugs. Based on a population PK analysis of Phase 1 studies with IR tablets in healthy subjects, concentrations of tramadol were approximately 20% higher in “poor metabolizers” versus “extensive metabolizers,” while M1 concentrations were 40% lower.

Drug Interaction Studies

Potential for Tramadol to Affect Other Drugs

In vitro studies indicate that tramadol is unlikely to inhibit the CYP3A4-mediated metabolism of other drugs when tramadol is administered concomitantly at therapeutic doses. Tramadol does not appear to induce its own metabolism in humans, since observed maximal plasma concentrations after multiple oral doses are higher than expected based on single-dose data.

CYP2D6 Inhibitors

In vitro drug interaction studies in human liver microsomes indicate that concomitant administration with inhibitors of CYP2D6 such as fluoxetine, paroxetine, and amitriptyline could result in some inhibition of the metabolism of tramadol (see PRECAUTIONS; Drug Interactions).

Quinidine

Tramadol is metabolized to active metabolite M1 by CYP2D6. Co-administration of quinidine, a selective inhibitor of CYP2D6, with tramadol extended-release tablets resulted in a 50% to 60% increase in tramadol exposure and a 50% to 60% decrease in M1 exposure. The clinical consequences of these findings are unknown.

To evaluate the effect of tramadol, a CYP2D6 substrate on quinidine, an in vitro drug interaction study in human liver microsomes was conducted. The results from this study indicate that tramadol has no effect on quinidine metabolism (see WARNINGS, PRECAUTIONS; Drug Interactions).

CYP3A4 Inhibitors and Inducers

Since tramadol is also metabolized by CYP3A4, administration of CYP3A4 inhibitors, such as ketoconazole and erythromycin, or CYP3A4 inducers, such as rifampin and St. John’s Wort, with tramadol HCl may affect the metabolism of tramadol leading to altered tramadol exposure (see WARNINGS, PRECAUTIONS; Drug Interactions).

Cimetidine

Concomitant administration of tramadol IR tablets with cimetidine, a weak CYP3A4 inhibitor, does not result in clinically significant changes in tramadol pharmacokinetics. No alteration of the tramadol HCl dosage regimen with cimetidine is recommended.

Carbamazepine

Carbamazepine, a CYP3A4 inducer, increases tramadol metabolism. Patients taking carbamazepine may have a significantly reduced analgesic effect of tramadol. Concomitant administration of tramadol HCl and carbamazepine is not recommended.

CLINICAL STUDIES

Tramadol HCl has been given in single oral doses of 50, 75 and 100 mg to patients with pain following surgical procedures and pain following oral surgery (extraction of impacted molars).

In single-dose models of pain following oral surgery, pain relief was demonstrated in some patients at doses of 50 mg and 75 mg. A dose of 100 mg tramadol HCl tended to provide analgesia superior to codeine sulfate 60 mg, but it was not as effective as the combination of aspirin 650 mg with codeine phosphate 60 mg.

Tramadol HCl has been studied in three long-term controlled trials involving a total of 820 patients, with 530 patients receiving tramadol HCl. Patients with a variety of chronic painful conditions were studied in double-blind trials of one to three months duration. Average daily doses of approximately 250 mg of tramadol HCl in divided doses were generally comparable to five doses of acetaminophen 300 mg with codeine phosphate 30 mg (TYLENOL with Codeine #3) daily, five doses of aspirin 325 mg with codeine phosphate 30 mg daily, or two to three doses of acetaminophen 500 mg with oxycodone hydrochloride 5 mg (TYLOX) daily.

Titration Trials

In a randomized, blinded clinical study with 129 to 132 patients per group, a 10-day titration to a daily tramadol HCl dose of 200 mg (50 mg four times per day), attained in 50 mg increments every 3 days, was found to result in fewer discontinuations due to dizziness or vertigo than titration over only 4 days or no titration. In a second study with 54 to 59 patients per group, patients who had nausea or vomiting when titrated over 4 days were randomized to re-initiate tramadol HCl therapy using slower titration rates.

A 16-day titration schedule, starting with 25 mg qAM and using additional doses in 25 mg increments every third day to 100 mg/day (25 mg four times per day), followed by 50 mg increments in the total daily dose every third day to 200 mg/day (50 mg four times per day), resulted in fewer discontinuations due to nausea or vomiting and fewer discontinuations due to any cause than did a 10-day titration schedule.

INDICATIONS AND USAGE

Tramadol HCl tablets are indicated for the management of pain in adults that is severe enough to require an opioid analgesic and for which alternative treatments are inadequate.

Limitations of Use

Because of the risks of addiction, abuse, and misuse with opioids, even at recommended doses (see WARNINGS), reserve tramadol HCl tablets for use in patients for whom alternative treatment options [e.g., non-opioid analgesics]:

- Have not been tolerated, or are not expected to be tolerated.
- Have not provided adequate analgesia, or are not expected to provide adequate analgesia.

CONTRAINDICATIONS

Tramadol HCl tablets contraindicated in patients with:

- Significant respiratory depression (see WARNINGS).
- Acute or severe bronchial asthma in an unmonitored setting or in the absence of resuscitative equipment (see WARNINGS).
- Known or suspected gastrointestinal obstruction, including paralytic ileus (see WARNINGS).
- Hypersensitivity to tramadol, any other component of this product or opioids (see WARNINGS).
- Concurrent use of monoamine oxidase inhibitors (MAOIs) or use of MAOIs within the last 14 days (see PRECAUTIONS; Drug Interactions).

WARNINGS

Addiction, Abuse, and Misuse

Tramadol HCl contains tramadol, a Schedule IV controlled substance. As an opioid, tramadol HCl exposes users to the risks of addiction, abuse, and misuse (see DRUG ABUSE AND DEPENDENCE).

Although the risk of addiction in any individual is unknown, it can occur in patients appropriately prescribed tramadol HCl. Addiction can occur at recommended dosages and if the drug is misused or abused.

Assess each patient’s risk for opioid addiction, abuse, or misuse prior to prescribing tramadol HCl, and monitor all patients receiving tramadol HCl for the development of these behaviors and conditions. Risks are increased in patients with a personal or family history of substance abuse (including drug or alcohol abuse or addiction) or mental illness (e.g., major depression). The potential for these risks should not, however, prevent the proper management of pain in any given patient. Patients at increased risk may be prescribed opioids such as tramadol HCl, but use in such patients necessitates intensive counseling about the risks and proper use of tramadol HCl along with intensive monitoring for signs of addiction, abuse, and misuse.

Opioids are sought by drug abusers and people with addiction disorders and are subject to criminal diversion. Consider these risks when prescribing or dispensing tramadol HCl. Strategies to reduce these risks include prescribing the drug in the smallest appropriate quantity and advising the patient on the proper disposal of unused drug (see PRECAUTIONS; Information for Patients). Contact local state professional licensing board or state controlled substances authority for information on how to prevent and detect abuse or diversion of this product.

Life-Threatening Respiratory Depression

Serious, life-threatening, or fatal respiratory depression has been reported with the use of opioids, even when used as recommended. Respiratory depression, if not immediately recognized and treated, may lead to respiratory arrest and death. Management of respiratory depression may include close observation, supportive measures, and use of opioid antagonists, depending on the patient’s clinical status (see OVERDOSAGE). Carbon dioxide (CO2) retention from opioid-induced respiratory depression can exacerbate the sedating effects of opioids.

While serious, life-threatening, or fatal respiratory depression can occur at any time during the use of tramadol HCl, the risk is greatest during the initiation of therapy or following a dosage increase. Monitor patients closely for respiratory depression, especially within the first 24 to 72 hours of initiating therapy with and following dosage increases of tramadol HCl.

To reduce the risk of respiratory depression, proper dosing and titration of tramadol HCl are essential (see DOSAGE AND ADMINISTRATION). Overestimating the tramadol HCl dosage when converting patients from another opioid product can result in a fatal overdose with the first dose.

Accidental ingestion of even one dose of tramadol HCl, especially by children, can result in respiratory depression and death due to an overdose of tramadol.

Neonatal Opioid Withdrawal Syndrome

Prolonged use of tramadol HCl during pregnancy can result in withdrawal in the neonate. Neonatal opioid withdrawal syndrome, unlike opioid withdrawal syndrome in adults, may be life-threatening if not recognized and treated, and requires management according to protocols developed by neonatology experts. Observe newborns for signs of neonatal opioid withdrawal syndrome and manage accordingly. Advise pregnant women using opioids for a prolonged period of the risk of neonatal opioid withdrawal syndrome and ensure that appropriate treatment will be available (see PRECAUTIONS; Information for Patients, Pregnancy).

Risks of Interactions with Drugs Affecting Cytochrome P450 Isoenzymes

The effects of concomitant use or discontinuation of cytochrome P450 3A4 inducers, 3A4 inhibitors, or 2D6 inhibitors on levels of tramadol and M1 from tramadol HCl are complex. Use of cytochrome P450 3A4 inducers, 3A4 inhibitors, or 2D6 inhibitors with tramadol HCl requires careful consideration of the effects on the parent drug, tramadol which is a weak serotonin and norepinephrine reuptake inhibitor and µ-opioid agonist, and the active metabolite, M1, which is more potent than tramadol in µ-opioid receptor binding (see PRECAUTIONS; Drug Interactions).

Risks of Concomitant Use or Discontinuation of Cytochrome P450 2D6 Inhibitors

The concomitant use of tramadol HCl with all cytochrome P450 2D6 inhibitors (e.g., amiodarone, quinidine) may result in an increase in tramadol plasma levels and a decrease in the levels of the active metabolite, M1. A decrease in M1 exposure in patients who have developed physical dependence to tramadol, may result in signs and symptoms of opioid withdrawal and reduced efficacy. The effect of increased tramadol levels may be an increased risk for serious adverse events including seizures and serotonin syndrome.

Discontinuation of a concomitantly used cytochrome P450 2D6 inhibitor may result in a decrease in tramadol plasma levels and an increase in active metabolite M1 levels, which could increase or prolong adverse reactions related to opioid toxicity and may cause potentially fatal respiratory depression.

Follow patients receiving tramadol HCl and any CYP2D6 inhibitor for the risk of serious adverse events including seizures and serotonin syndrome, signs and symptoms that may reflect opioid toxicity, and opioid withdrawal when tramadol HCl is used in conjunction with inhibitors of CYP2D6 (see PRECAUTIONS; Drug Interactions).

Cytochrome P450 3A4 Interaction

The concomitant use of tramadol HCl with cytochrome P450 3A4 inhibitors, such as macrolide antibiotics (e.g., erythromycin), azole-antifungal agents (e.g., ketoconazole), and protease inhibitors (e.g., ritonavir) or discontinuation of a cytochrome P450 3A4 inducer such as rifampin, carbamazepine, and phenytoin, may result in an increase in tramadol plasma concentrations, which could increase or prolong adverse reactions, increase the risk for serious adverse events including seizures and serotonin syndrome, and may cause potentially fatal respiratory depression.

The concomitant use of tramadol HCl with all cytochrome P450 3A4 inducers or discontinuation of a cytochrome P450 3A4 inhibitor may result in lower tramadol levels. This may be associated with a decrease in efficacy, and in some patients, may result in signs and symptoms of opioid withdrawal.

Follow patients receiving tramadol HCl and any CYP3A4 inhibitor or inducer for the risk for serious adverse events including seizures and serotonin syndrome, signs and symptoms that may reflect opioid toxicity and opioid withdrawal when tramadol HCl is used in conjunction with inhibitors and inducers of CYP3A4 (see PRECAUTIONS; Drug Interactions).

Risks from Concomitant Use with Benzodiazepines or Other CNS Depressants

Profound sedation, respiratory depression, coma, and death may result from the concomitant use of tramadol HCl with benzodiazepines or other CNS depressants (e.g., non-benzodiazepine sedatives/hypnotics, anxiolytics, tranquilizers, muscle relaxants, general anesthetics, antipsychotics, other opioids, alcohol). Because of these risks, reserve concomitant prescribing of these drugs for use in patients for whom alternative treatment options are inadequate.

Observational studies have demonstrated that concomitant use of opioid analgesics and benzodiazepines increases the risk of drug-related mortality compared to use of opioid analgesics alone. Because of similar pharmacological properties, it is reasonable to expect similar risk with the concomitant use of other CNS depressant drugs with opioid analgesics (see PRECAUTIONS; Drug Interactions).

If the decision is made to prescribe a benzodiazepine or other CNS depressant concomitantly with an opioid analgesic, prescribe the lowest effective dosages and minimum durations of concomitant use. In patients already receiving an opioid analgesic, prescribe a lower initial dose of the benzodiazepine or other CNS depressant than indicated in the absence of an opioid, and titrate based on clinical response. If an opioid analgesic is initiated in a patient already taking a benzodiazepine or other CNS depressant, prescribe a lower initial dose of the opioid analgesic, and titrate based on clinical response. Follow patients closely for signs and symptoms of respiratory depression and sedation.

Advise both patients and caregivers about the risks of respiratory depression and sedation when tramadol HCl is used with benzodiazepines or other CNS depressants (including alcohol and illicit drugs). Advise patients not to drive or operate heavy machinery until the effects of concomitant use of the benzodiazepine or other CNS depressant have been determined. Screen patients for risk of substance use disorders, including opioid abuse and misuse, and warn them of the risk for overdose and death associated with the use of additional CNS depressants including alcohol and illicit drugs (see PRECAUTIONS; Drug Interactions, Information for Patients/Caregivers).

Serotonin Syndrome Risk

Cases of serotonin syndrome, a potentially life-threatening condition, have been reported with the use of tramadol, particularly during concomitant use with serotonergic drugs. Serotonergic drugs include selective serotonin reuptake inhibitors (SSRIs), serotonin and norepinephrine reuptake inhibitors (SNRIs), tricyclic antidepressants (TCAs), triptans, 5-HT3 receptor antagonists, drugs that affect the serotonergic neurotransmitter system (e.g., mirtazapine, trazodone, tramadol), and drugs that impair metabolism of serotonin (including MAO inhibitors, both those intended to treat psychiatric disorders and also others, such as linezolid and intravenous methylene blue) (see PRECAUTIONS; Drug Interactions). This may occur within the recommended dosage range.

Serotonin syndrome symptoms may include mental status changes (e.g., agitation, hallucinations, coma), autonomic instability (e.g., tachycardia, labile blood pressure, hyperthermia), neuromuscular aberrations (e.g., hyperreflexia, incoordination, rigidity), and/or gastrointestinal symptoms (e.g., nausea, vomiting, diarrhea). The onset of symptoms generally occurs within several hours to a few days of concomitant use, but may occur later than that. Discontinue tramadol HCl if serotonin syndrome is suspected.

Increased Risk of Seizure

Seizures have been reported in patients receiving tramadol HCl within the recommended dosage range. Spontaneous post-marketing reports indicate that seizure risk is increased with doses of tramadol HCl above the recommended range. Concomitant use of tramadol HCl increases the seizure risk in patients taking:

- Selective serotonin re-uptake inhibitors (SSRI antidepressants or anorectics),
- Tricyclic antidepressants (TCAs), and other tricyclic compounds (e.g., cyclobenzaprine, promethazine, etc.), or
- Other opioids,
- MAO inhibitors (see also WARNINGS, Serotonin Syndrome Risk),
- Neuroleptics, or
- Other drugs that reduce the seizure threshold.

Risk of seizure may also increase in patients with epilepsy, those with a history of seizures, or in patients with a recognized risk for seizure (such as head trauma, metabolic disorders, alcohol and drug withdrawal, CNS infections). In tramadol HCl overdose, naloxone administration may increase the risk of seizure.

Suicide Risk

- Do not prescribe tramadol HCl for patients who are suicidal or addiction-prone. Consideration should be given to the use of non-narcotic analgesics in patients who are suicidal or depressed (see DRUG ABUSE AND DEPENDENCE).
- Prescribe tramadol HCl tablets with caution for patients with a history of misuse and/or are currently taking CNS-active drugs including tranquilizers or antidepressant drugs, alcohol in excess, and patients who suffer from emotional disturbance or depression (see PRECAUTIONS; Drug Interactions).
- Inform patients not to exceed the recommended dose and to limit their intake of alcohol (see DOSAGE AND ADMINISTRATION).

Adrenal Insufficiency

Cases of adrenal insufficiency have been reported with opioid use, more often following greater than one month of use. Presentation of adrenal insufficiency may include non-specific symptoms and signs including nausea, vomiting, anorexia, fatigue, weakness, dizziness, and low blood pressure. If adrenal insufficiency is suspected, confirm the diagnosis with diagnostic testing as soon as possible. If adrenal insufficiency is diagnosed, treat with physiologic replacement doses of corticosteroids. Wean the patient off of the opioid to allow adrenal function to recover and continue corticosteroid treatment until adrenal function recovers. Other opioids may be tried as some cases reported use of a different opioid without recurrence of adrenal insufficiency. The information available does not identify any particular opioids as being more likely to be associated with adrenal insufficiency.

Life-Threatening Respiratory Depression in Patients with Chronic Pulmonary Disease or in Elderly, Cachectic, or Debilitated Patients

The use of tramadol HCl in patients with acute or severe bronchial asthma in an unmonitored setting or in the absence of resuscitative equipment is contraindicated.

Patients with Chronic Pulmonary Disease: tramadol HCl-treated patients with significant chronic obstructive pulmonary disease or cor pulmonale, and those with a substantially decreased respiratory reserve, hypoxia, hypercapnia, or pre-existing respiratory depression are at increased risk of decreased respiratory drive including apnea, even at recommended dosages of tramadol HCl (see WARNINGS).

Elderly, Cachectic, or Debilitated Patients: Life-threatening respiratory depression is more likely to occur in elderly, cachectic, or debilitated patients because they may have altered pharmacokinetics or altered clearance compared to younger, healthier patients (see WARNINGS).

Monitor such patients closely, particularly when initiating and titrating tramadol HCl and when tramadol HCl is given concomitantly with other drugs that depress respiration (see WARNINGS). Alternatively, consider the use of non-opioid analgesics in these patients.

Severe Hypotension

Tramadol HCl may cause severe hypotension including orthostatic hypotension and syncope in ambulatory patients. There is increased risk in patients whose ability to maintain blood pressure has already been compromised by a reduced blood volume or concurrent administration of certain CNS depressant drugs (e.g. phenothiazines or general anesthetics) (see PRECAUTIONS; Drug Interactions). Monitor these patients for signs of hypotension after initiating or titrating the dosage of tramadol HCl. In patients with circulatory shock, tramadol HCl may cause vasodilation that can further reduce cardiac output and blood pressure. Avoid the use of tramadol HCl in patients with circulatory shock.

Risks of use in Patients with Increased Intracranial Pressure, Brain Tumors, Head Injury, or Impaired Consciousness

In patients who may be susceptible to the intracranial effects of CO2 retention (e.g., those with evidence of increased intracranial pressure or brain tumors), tramadol HCl may reduce respiratory drive, and the resultant CO2 retention can further increase intracranial pressure. Monitor such patients for signs of sedation and respiratory depression, particularly when initiating therapy with tramadol HCl.

Opioids may also obscure the clinical course in a patient with a head injury. Avoid the use of tramadol HCl in patients with impaired consciousness or coma.

Risks of use in Patients with Gastrointestinal Conditions

Tramadol HCl is contraindicated in patients with known or suspected gastrointestinal obstruction, including paralytic ileus (see CONTRAINDICATIONS).

The tramadol in tramadol HCl may cause spasm of the sphincter of Oddi. Opioids may cause increases in serum amylase. Monitor patients with biliary tract disease, including acute pancreatitis for worsening symptoms.

Anaphylaxis and Other Hypersensitivity Reactions

Serious and rarely fatal anaphylactoid reactions have been reported in patients receiving therapy with tramadol HCl. When these events do occur it is often following the first dose.

Other reported allergic reactions include pruritus, hives, bronchospasm, angioedema, toxic epidermal necrolysis and Stevens-Johnson syndrome. Patients with a history of anaphylactoid reactions to codeine and other opioids may be at increased risk and therefore should not receive tramadol HCl (see CONTRAINDICATIONS). If anaphylaxis or other hypersensitivity occurs, stop administration of tramadol HCl immediately, discontinue tramadol HCl permanently, and do not rechallenge with any formulation of tramadol. Advise patients to seek immediate medical attention if they experience any symptoms of a hypersensitivity reaction (see CONTRAINDICATIONS, PRECAUTIONS; Information for Patients).

Withdrawal

Avoid the use of mixed agonist/antagonist (e.g, pentazocine, nalbuphine, and butorphanol) or partial agonist (e.g., buprenorphine) analgesics in patients who are receiving a full opioid agonist analgesic, including tramadol HCl. In these patients, mixed agonist/antagonist and partial agonist analgesics may reduce the analgesic effect and/or precipitate withdrawal symptoms.

When discontinuing tramadol HCl in a physically-dependent patient, gradually taper the dosage (see DOSAGE AND ADMINISTRATION). Do not abruptly discontinue tramadol HCl in these patients (see DRUG ABUSE AND DEPENDENCE).

Risks of Driving and Operating Machinery

Tramadol HCl may impair the mental or physical abilities needed to perform potentially hazardous activities such as driving a car or operating machinery. Warn patients not to drive or operate dangerous machinery unless they are tolerant to the effects of tramadol HCl and know how they will react to the medication.

PRECAUTIONS

Renal and Hepatic Disease

Impaired renal function results in a decreased rate and extent of excretion of tramadol and its active metabolite, M1. In patients with creatinine clearances of less than 30 mL/min, dosing reduction is recommended (see DOSAGE AND ADMINISTRATION). Metabolism of tramadol and M1 is reduced in patients with advanced cirrhosis of the liver. In cirrhotic patients, dosing reduction is recommended (see DOSAGE AND ADMINISTRATION).

With the prolonged half-life in these conditions, achievement of steady-state is delayed, so that it may take several days for elevated plasma concentrations to develop.

Information for Patients

Advise the patient to read the FDA-approved patient labeling (Medication Guide).

Addiction, Abuse, and Misuse

Inform patients that the use of tramadol HCl, even when taken as recommended, can result in addiction, abuse, and misuse, which can lead to overdose and death (see WARNINGS). Instruct patients not to share tramadol HCl with others and to take steps to protect tramadol HCl from theft or misuse.

Life-Threatening Respiratory Depression

Inform patients of the risk of life-threatening respiratory depression, including information that the risk is greatest when starting tramadol HCl or when the dosage is increased, and that it can occur even at recommended dosages (see WARNINGS). Advise patients how to recognize respiratory depression and to seek medical attention if breathing difficulties develop.

Accidental Ingestion

Inform patients that accidental ingestion, especially by children, may result in respiratory depression or death (see WARNINGS). Instruct patients to take steps to store tramadol HCl securely and to dispose of unused tramadol HCl in accordance with the local state guidelines and/or regulations.

Interactions with Benzodiazepines and Other CNS Depressants

Inform patients and caregivers that potentially fatal additive effects may occur if tramadol HCl is used with benzodiazepines, CNS depressants, including alcohol, or some illicit drugs and not to use these concomitantly unless supervised by a health care provider (see WARNINGS, PRECAUTIONS; Drug Interactions).

Serotonin Syndrome

Inform patients that opioids could cause a rare but potentially life-threatening condition resulting from concomitant administration of serotonergic drugs. Warn patients of the symptoms of serotonin syndrome, and to seek medical attention right away if symptoms develop. Instruct patients to inform their healthcare provider if they are taking, or plan to take serotonergic medications (see WARNINGS).

MAOI Interaction

Inform patients not to take tramadol HCl while using any drugs that inhibit monoamine oxidase. Patients should not start MAOIs while taking tramadol HCl (see PRECAUTIONS: Drug Interactions).

Seizures

Inform patients that tramadol HCl may cause seizures with concomitant use of serotonergic agents (including SSRIs, SNRIs, and triptans) or drugs that significantly reduce the metabolic clearance of tramadol (see WARNINGS).

Adrenal Insufficiency

Inform patients that opioids could cause adrenal insufficiency, a potentially life-threatening condition. Adrenal insufficiency may present with non-specific symptoms and signs such as nausea, vomiting, anorexia, fatigue, weakness, dizziness, and low blood pressure. Advise patients to seek medical attention if they experience a constellation of these symptoms (see WARNINGS).

Important Administration Instructions

Instruct patients how to properly take tramadol HCl (see DOSAGE AND ADMINISTRATION, WARNINGS).

- Advise patients not to adjust the dose of tramadol HCl without consulting with a physician or other healthcare professional.
- If patients have been receiving treatment with tramadol HCl for more than a few weeks and cessation of therapy is indicated, counsel them on the importance of safely tapering the dose as abrupt discontinuation of the medication could precipitate withdrawal symptoms. Provide a dose schedule to accomplish a gradual discontinuation of the medication (see DOSAGE AND ADMINISTRATION).

Hypotension

Inform patients that tramadol HCl may cause orthostatic hypotension and syncope. Instruct patients how to recognize symptoms of low blood pressure and how to reduce the risk of serious consequences should hypotension occur (e.g., sit or lie down, carefully rise from a sitting or lying position) (see WARNINGS).

Anaphylaxis

Inform patients that anaphylaxis has been reported with ingredients contained in tramadol HCl tablets. Advise patients how to recognize such a reaction and when to seek medical attention (see CONTRAINDICATIONS, ADVERSE REACTIONS).

Pregnancy

Neonatal Opioid Withdrawal Syndrome

Inform female patients of reproductive potential that prolonged use of tramadol HCl during pregnancy can result in neonatal opioid withdrawal syndrome, which may be life-threatening if not recognized and treated and that the patient should inform their healthcare provider if they have used opioids at any time during their pregnancy, especially near the time of birth (see WARNINGS, PRECAUTIONS; Labor or Delivery).

Embryo-Fetal Toxicity

Inform female patients of reproductive potential that tramadol HCl may cause fetal harm and to inform the healthcare provider of a known or suspected pregnancy (see PRECAUTONS; Pregnancy).

Lactation

Advise nursing mothers to monitor infants for increased sleepiness (more than usual), breathing difficulties, or limpness. Instruct nursing mothers to seek immediate medical care if they notice these signs (see PRECAUTIONS; Lactation).

Infertility

Inform patients that chronic use of opioids may cause reduced fertility. It is not known whether these effects on fertility are reversible (see PRECAUTIONS).

Driving or Operating Heavy Machinery

Inform patients that tramadol HCl may impair the ability to perform potentially hazardous activities such as driving a car or operating heavy machinery. Advise patients not to perform such tasks until they know how they will react to the medication (see WARNINGS).

Constipation

Advise patients of the potential for severe constipation, including management instructions and when to seek medical attention (see ADVERSE REACTIONS).

Disposal of Unused Tramadol HCl

Advise patients to throw the unused tramadol HCl in the household trash following these steps. 1) Remove the drugs from their original containers and mix with an undesirable substance, such as used coffee grounds or kitty litter (this makes the drug less appealing to children and pets, and unrecognizable to people who may intentionally go through the trash seeking drugs). 2) Place the mixture in a sealable bag, empty can, or other container to prevent the drug from leaking or breaking out of a garbage bag.

Maximum single-dose and 24-hour dose

Advise patients not to exceed the single-dose and 24-hour dose limit and the time interval between doses, since exceeding these recommendations can result in respiratory depression, seizures and death (see DOSAGE AND ADMINISTRATION; WARNINGS).

Drug Interactions

Inhibitors of CYP2D6

The concomitant use of tramadol HCl and CYP2D6 inhibitors, such as quinidine, fluoxetine, paroxetine and bupropion, may result in an increase in the plasma concentration of tramadol and a decrease in the plasma concentration of M1, particularly when an inhibitor is added after a stable dose of tramadol HCl is achieved. Since M1 is a more potent µ-opioid agonist, decreased M1 exposure could result in decreased therapeutic effects, and may result in signs and symptoms of opioid withdrawal in patients who had developed physical dependence to tramadol. Increased tramadol exposure can result in increased or prolonged therapeutic effects and increased risk for serious adverse events including seizures and serotonin syndrome.

After stopping a CYP2D6 inhibitor, as the effects of the inhibitor decline, the tramadol plasma concentration will decrease and the M1 plasma concentration will increase which could increase or prolong therapeutic effects but also increase adverse reactions related to opioid toxicity, and may cause potentially fatal respiratory depression (see CLINICAL PHARMACOLOGY)

If concomitant use of a CYP2D6 inhibitor is necessary, follow patients closely for adverse reactions including opioid withdrawal, seizures, and serotonin syndrome.

If a CYP2D6 inhibitor is discontinued, consider lowering tramadol HCl dosage until stable drug effects are achieved. Follow patients closely for adverse events including respiratory depression and sedation.

Use With Quinidine

Quinidine is a selective inhibitor of CYP2D6, so that concomitant administration of quinidine and tramadol HCl results in increased concentrations of tramadol and reduced concentrations of M1. The clinical consequences of these findings are unknown.

Inhibitors of CYP3A4

The concomitant use of tramadol HCl and CYP3A4 inhibitors, such as macrolide antibiotics (e.g., erythromycin), azole-antifungal agents (e.g. ketoconazole), protease inhibitors (e.g., ritonavir), can increase the plasma concentration of tramadol, and may result in a greater amount of metabolism via CYP2D6 and greater levels of M1. Follow patients closely for increased risk of serious adverse events including seizures and serotonin syndrome, and adverse reactions related to opioid toxicity including potentially fatal respiratory depression, particularly when a CYP3A4 inhibitor is added after a stable dose of tramadol HCl is achieved.

After stopping a CYP3A4 inhibitor, as the effects of the inhibitor decline, the tramadol plasma concentration will decrease (see CLINICAL PHARMACOLOGY), resulting in decreased opioid efficacy or a withdrawal syndrome in patients who had developed physical dependence to tramadol.

If concomitant use is necessary, consider dosage reduction of tramadol HCl until stable drug effects are achieved. Follow patients closely for seizures and serotonin syndrome, and signs of respiratory depression and sedation at frequent intervals. If a CYP3A4 inhibitor is discontinued, consider increasing the tramadol HCl dosage until stable drug effects are achieved and follow patients for signs and symptoms of opioid withdrawal.

CYP3A4 Inducers

The concomitant use of tramadol HCl and CYP3A4 inducers, such as rifampin, carbamazepine and phenytoin, can decrease the plasma concentration of tramadol resulting in decreased efficacy or onset of a withdrawal syndrome in patients who have developed physical dependence to tramadol (see WARNINGS).

After stopping a CYP3A4 inducer, as the effects of the inducer decline, the tramadol plasma concentration will increase, which could increase or prolong both the therapeutic effects and adverse reactions, and may cause seizures and serotonin syndrome, and potentially fatal respiratory depression.

Use With Carbamazepine

Patients taking carbamazepine, a CYP3A4 inducer, may have a significantly reduced analgesic effect of tramadol. Because carbamazepine increases tramadol metabolism and because of the seizure risk associated with tramadol, concomitant administration of tramadol HCl and carbamazepine is not recommended.

Benzodiazepines and Other Central Nervous System (CNS) Depressants

Due to additive pharmacologic effects, the concomitant use of benzodiazepines or other CNS depressants, including alcohol, increases the risk of respiratory depression, profound sedation, coma, and death. Examples of other CNS depressants include other sedatives/hypnotics, anxiolytics, tranquilizers, muscle relaxants, general anesthetics, antipsychotics, other opioids, and some illicit drugs.

Reserve concomitant prescribing of these drugs for use in patients for whom alternative treatment options are inadequate. Limit the treatment to the minimum effective dosages and durations. Follow patients closely for signs of respiratory depression and sedation (see WARNINGS).

Serotonergic Drugs

The concomitant use of opioids with other drugs that affect the serotonergic neurotransmitter system has resulted in serotonin syndrome. Examples of these drugs include, selective serotonin reuptake inhibitors (SSRIs), serotonin and norepinephrine reuptake inhibitors (SNRIs), tricyclic antidepressants (TCAs), triptans, 5-HT3 receptor antagonists, drugs that effect the serotonin neurotransmitter system (e.g., mirtazapine, trazodone), monoamine oxidase (MAO) inhibitors (used to treat psychiatric disorders and also others, such as linezolid and intravenous methylene blue).

If concomitant use is warranted, carefully observe the patient, particularly during treatment initiation and dose adjustment. Discontinue tramadol HCl immediately if serotonin syndrome is suspected.

Monoamine Oxidase Inhibitors (MAOIs)

Do not use tramadol HCl in patients taking MAOIs or within 14 days of stopping such treatment.

MAOI interactions with opioids may manifest as serotonin syndrome (see WARNINGS) or opioid toxicity (e.g., respiratory depression, coma) (see WARNINGS). Examples of these drugs include, phenelzine, tranylcypromine, linezolid.

Digoxin

Post-marketing surveillance has revealed rare reports of digoxin toxicity. Follow patients for signs of digoxin toxicity and adjust dosage of digoxin as needed.

Warfarin

Post-marketing surveillance of tramadol has revealed rare reports of alteration of warfarin effect, including elevation of prothrombin times. Monitor the prothrombin time of patients on warfarin for signs of an interaction and adjust the dosage of warfarin as needed.

Mixed Agonist/Antagonist and Partial Agonist Opioid Analgesics

Mixed agonist/antagonist and partial agonist opioid analgesics may reduce the analgesic effect of tramadol HCl and/or precipitate withdrawal symptoms. Examples of these drugs include butorphanol, nalbuphine, pentazocine and buprenorphine. Avoid concomitant use of these drugs.

Muscle Relaxants

Tramadol may enhance the neuromuscular blocking action of skeletal muscle relaxants and produce an increased degree of respiratory depression. Monitor patients for signs of respiratory depression that may be greater than otherwise expected and decrease the dosage of tramadol HCl and/or the muscle relaxant as necessary.

Diuretics

Opioids can reduce the efficacy of diuretics by inducing the release of antidiuretic hormone. Monitor patients for signs of diminished diuresis and/or effects on blood pressure and increase the dosage of the diuretic as needed.

Anticholinergic Drugs

The concomitant use of anticholinergic drugs may increase risk of urinary retention and/or severe constipation, which may lead to paralytic ileus. Monitor patients for signs of urinary retention or reduced gastric motility when tramadol HCl is used concomitantly with anticholinergic drugs.

Carcinogenesis, Mutagenesis, Impairment of Fertility

Carcinogenesis

A slight, but statistically significant, increase in two common murine tumors, pulmonary and hepatic, was observed in an NMRI mouse carcinogenicity study, particularly in aged mice. Mice were dosed orally up to 30 mg/kg in the drinking water (0.36 times the maximum recommended human daily dosage or MRHD) for approximately two years, although the study was not done with the Maximum Tolerated Dose. This finding is not believed to suggest risk in humans. No evidence of carcinogenicity was noted in a rat 2-year carcinogenicity study testing oral doses of up to 30 mg/kg in the drinking water, 0.73 times the MRHD).

Mutagenesis

Tramadol was mutagenic in the presence of metabolic activation in the mouse lymphoma assay. Tramadol was not mutagenic in the in vitro bacterial reverse mutation assay using Salmonella and E. coli (Ames), the mouse lymphoma assay in the absence of metabolic activation, the in vitro chromosomal aberration assay, or the in vivo micronucleus assay in bone marrow.

Impairment of Fertility

No effects on fertility were observed for tramadol at oral dose levels up to 50 mg/kg in male rats and 75 mg/kg in female rats. These dosages are 1.2 and 1.8 times the maximum recommended human daily dose based on body surface area, respectively.

Pregnancy

Risk Summary

Prolonged use of opioid analgesics during pregnancy may cause neonatal opioid withdrawal syndrome. Available data with tramadol HCl in pregnant women are insufficient to inform a drug-associated risk for major birth defects and miscarriage.

In animal reproduction studies, tramadol administration during organogenesis decreased fetal weights and reduced ossification in mice, rats, and rabbits at 1.4, 0.6, and 3.6 times the maximum recommended human daily dosage (MRHD). Tramadol decreased pup body weight and increased pup mortality at 1.2 and 1.9 times the MRHD [see Data]. Based on animal data, advise pregnant women of the potential risk to a fetus.

The estimated background risk of major birth defects and miscarriage for the indicated population is unknown. All pregnancies have a background risk of birth defect, loss, or other adverse outcomes. In the U.S. general population, the estimated background risk of major birth defects and miscarriage in clinically recognized pregnancies is 2% to 4% and 15% to 20%, respectively.

Clinical Considerations

Neonatal Adverse Reactions

Prolonged use of opioid analgesics during pregnancy for medical or nonmedical purposes can result in respiratory depression and physical dependence in the neonate and neonatal opioid withdrawal syndrome shortly after birth.

Neonatal opioid withdrawal syndrome can present as irritability, hyperactivity and abnormal sleep pattern, high pitched cry, tremor, vomiting, diarrhea and failure to gain weight. The onset, duration, and severity of neonatal opioid withdrawal syndrome vary based on the specific opioid used, duration of use, timing and amount of last maternal use, and rate of elimination of the drug by the newborn. Observe newborns for symptoms and signs of neonatal opioid withdrawal syndrome and manage accordingly (see WARNINGS).

Neonatal seizures, neonatal withdrawal syndrome, fetal death and still birth have been reported during post-marketing.

Labor and Delivery

Tramadol HCl is not recommended for use in pregnant women during or immediately prior to labor, when other analgesic techniques are more appropriate. Opioids cross the placenta and may induce dependency of the fetus, acute respiratory depression in the newborn and/or psycho-physiologic effects associated with opioid exposure and withdrawal. An opioid antagonist, such as naloxone, must be available for reversal of opioid-induced respiratory depression in the neonate. Monitor newborns exposed to opioid analgesics during labor for signs of excess sedation and respiratory depression.

Use of opioid analgesics, including tramadol HCl, may impact the duration of labor due to inhibitory actions on uterine contractions or facilitatory actions on cervical dilation.

Tramadol has been shown to cross the placenta. The mean ratio of serum tramadol in the umbilical veins compared to maternal veins was 0.83 for 40 women given tramadol during labor.

The effect of tramadol HCl, if any, on the later growth, development, and functional maturation of the child is unknown.

Data

Animal Data

Tramadol has been shown to be embryotoxic and fetotoxic in mice, (120 mg/kg), rats (25 mg/kg) and rabbits (75 mg/kg) at maternally toxic dosages, but was not teratogenic at these dose levels. These doses on a mg/m^2 basis are 1.4, 0.6, and 3.6 times the maximum recommended human daily dosage (MRHD) for mouse, rat and rabbit, respectively.

No drug-related teratogenic effects were observed in progeny of mice (up to 140 mg/kg), rats (up to 80 mg/kg) or rabbits (up to 300 mg/kg) treated with tramadol by various routes. Embryo and fetal toxicity consisted primarily of decreased fetal weights, decreased skeletal ossification and increased supernumerary ribs at maternally toxic dose levels. Transient delays in developmental or behavioral parameters were also seen in pups from rat dams allowed to deliver. Embryo and fetal lethality were reported only in one rabbit study at 300 mg/kg, a dose that would cause extreme maternal toxicity in the rabbit. The dosages listed for mouse, rat and rabbit are 1.7, 1.9 and 14.6 times the MRHD, respectively.

Tramadol was evaluated in pre- and post-natal studies in rats. Progeny of dams receiving oral (gavage) dose levels of 50 mg/kg (1.2 times the MRHD) or greater had decreased weights, and pup survival was decreased early in lactation at 80 mg/kg (1.9 times the MRHD).

Nursing Mothers

Tramadol HCl is not recommended for obstetrical preoperative medication or for post-delivery analgesia in nursing mothers because its safety in infants and newborns has not been studied. Following a single IV 100 mg dose of tramadol, the cumulative excretion in breast milk within 16 hours postdose was 100 mcg of tramadol (0.1% of the maternal dose) and 27 mcg of M1.

Because of the potential for serious adverse reactions, including excess sedation and respiratory depression in a breastfed infant, advise patients that breastfeeding is not recommended during treatment with tramadol HCl.

Monitor infants exposed to tramadol HCl through breast milk for excess sedation and respiratory depression. Withdrawal symptoms can occur in breastfed infants when maternal administration of an opioid analgesic is stopped, or when breast-feeding is stopped.

Females and Males of Reproductive Potential

Infertility

Due to effects of androgen deficiency, chronic use of opioids may cause reduced fertility in females and males of reproductive potential. It is not known whether these effects on fertility are reversible (see ADVERSE REACTIONS).

Pediatric Use

The safety and efficacy of tramadol HCl in patients under 16 years of age have not been established. The use of tramadol HCl in the pediatric population is not recommended.

Geriatric Use

A total of 455 elderly (65 years of age or older) subjects were exposed to tramadol HCl in controlled clinical trials. Of those, 145 subjects were 75 years of age and older.

In studies including geriatric patients, treatment-limiting adverse events were higher in subjects over 75 years of age compared to those under 65 years of age. Specifically, 30% of those over 75 years of age had gastrointestinal treatment-limiting adverse events compared to 17% of those under 65 years of age. Constipation resulted in discontinuation of treatment in 10% of those over 75.

Respiratory depression is the chief risk for elderly patients treated with opioids, and has occurred after large initial doses were administered to patients who were not opioid-tolerant or when opioids were co-administered with other agents that depress respiration. Titrate the dosage of tramadol HCl slowly in geriatric patients and monitor closely for signs of central nervous system and respiratory depression (see WARNINGS).

Tramadol is known to be substantially excreted by the kidney, and the risk of adverse reactions to this drug may be greater in patients with impaired renal function. Because elderly patients are more likely to have decreased renal function, care should be taken in dose selection, and it may be useful to monitor renal function.

ADVERSE REACTIONS

The following serious adverse reactions are described, or described in greater detail, in other sections:

- Addiction, Abuse, and Misuse (see WARNINGS)
- Life-Threatening Respiratory Depression (see WARNINGS)
- Neonatal Opioid Withdrawal Syndrome (see WARNINGS)
- Interactions with Benzodiazepines or Other CNS Depressants (see WARNINGS)
- Serotonin Syndrome (see WARNINGS)
- Seizures (see WARNINGS)
- Suicide (see WARNINGS)
- Adrenal Insufficiency (see WARNINGS)
- Severe Hypotension (see WARNINGS)
- Gastrointestinal Adverse Reactions (see WARNINGS)
- Hypersensitivity Reactions (see WARNINGS)
- Withdrawal (see WARNINGS)

Clinical Trials Experience

Because clinical trials are conducted under widely varying conditions, adverse reaction rates observed in the clinical trials of a drug cannot be directly compared to rates in the clinical trials of another drug and may not reflect the rates observed in practice.

Tramadol HCl was administered to 550 patients during the double-blind or open-label extension periods in U.S. studies of chronic nonmalignant pain. Of these patients, 375 were 65 years old or older. Table 2 reports the cumulative incidence rate of adverse reactions by 7, 30 and 90 days for the most frequent reactions (5% or more by 7 days).

The most frequently reported events were in the central nervous system and gastrointestinal system. Although the reactions listed in the table are felt to be probably related to tramadol HCl administration, the reported rates also include some events that may have been due to underlying disease or concomitant medication. The overall incidence rates of adverse experiences in these trials were similar for tramadol HCl and the active control groups, TYLENOL with Codeine #3 (acetaminophen 300 mg with codeine phosphate 30 mg), and aspirin 325 mg with codeine phosphate 30 mg, however, the rates of withdrawals due to adverse events appeared to be higher in the tramadol HCl groups.

Table 2: Cumulative Incidence of Adverse Reactions for Tramadol HClin Chronic Trials of

Nonmalignant Pain (N=427)

 | Up to 7 Days | Up to 30 Days | Up to 90 Days
Dizziness/Vertigo | 26% | 31% | 33%
Nausea | 24% | 34% | 40%
Constipation | 24% | 38% | 46%
Headache | 18% | 26% | 32%
Somnolence | 16% | 23% | 25%
Vomiting | 9% | 13% | 17%
Pruritus | 8% | 10% | 11%
“CNS Stimulation”^1 | 7% | 11% | 14%
Asthenia | 6% | 11% | 12%
Sweating | 6% | 7% | 9%
Dyspepsia | 5% | 9% | 13%
Dry Mouth | 5% | 9% | 10%
Diarrhea | 5% | 6% | 10%

^1 “CNS Stimulation” is a composite of nervousness, anxiety, agitation, tremor, spasticity, euphoria, emotional lability and hallucinations

Incidence 1% to less than 5% possibly causally related:

The following lists adverse reactions that occurred with an incidence of 1% to less than 5% in clinical trials, and for which the possibility of a causal relationship with tramadol HCl exists.

Body as a Whole: Malaise.

Cardiovascular: Vasodilation.

Central Nervous System: Anxiety, Confusion, Coordination disturbance, Euphoria, Miosis, Nervousness, Sleep disorder.

Gastrointestinal: Abdominal pain, Anorexia, Flatulence.

Musculoskeletal: Hypertonia.

Skin: Rash.

Special Senses: Visual disturbance.

Urogenital: Menopausal symptoms, Urinary frequency, Urinary retention.

Incidence less than 1%, possibly causally related:

The following lists adverse reactions that occurred with an incidence of less than 1% in clinical trials of tramadol and/or reported in post-marketing experience with tramadol-containing products.

Body as a Whole: Accidental injury, Allergic reaction, Anaphylaxis, Death, Suicidal tendency, Weight loss, Serotonin syndrome (mental status change, hyperreflexia, fever, shivering, tremor, agitation, diaphoresis, seizures and coma).

Cardiovascular: Orthostatic hypotension, Syncope, Tachycardia.

Central Nervous System: Abnormal gait, Amnesia, Cognitive dysfunction, Delirium, Depression, Difficulty in concentration, Hallucinations, Movement disorder, Paresthesia, Seizure, Speech disorder, Tremor.

Metabolism and Nutrition Disorders: Cases of hypoglycemia have been reported very rarely in patients taking tramadol. Most reports were in patients with predisposing risk factors, including diabetes or renal insufficiency, or in elderly patients.

Respiratory: Dyspnea.

Skin: Stevens-Johnson syndrome/Toxic epidermal necrolysis, Urticaria, Vesicles.

Special Senses: Dysgeusia, Mydriasis.

Urogenital: Dysuria, Menstrual disorder.

Other adverse experiences, causal relationship unknown:

A variety of other adverse events were reported infrequently in patients taking tramadol HCl during clinical trials and/or reported in post-marketing experience. A causal relationship between tramadol HCl and these events has not been determined. However, the most significant events are listed below as alerting information to the physician.

Cardiovascular: Abnormal ECG, Hypertension, Hypotension, Myocardial ischemia, Palpitations, Pulmonary edema, Pulmonary embolism.

Central Nervous System: Migraine.

Gastrointestinal: Gastrointestinal bleeding, Hepatitis, Stomatitis, Liver failure.

Laboratory Abnormalities: Creatinine increase, Elevated liver enzymes, Hemoglobin decrease, Proteinuria.

Sensory: Cataracts, Deafness, Tinnitus.

Postmarketing Experience

Serotonin syndrome: Cases of serotonin syndrome, a potentially life-threatening condition, have been reported during concomitant use of opioids with serotonergic drugs.

Adrenal insufficiency: Cases of adrenal insufficiency have been reported with opioid use, more often following greater than one month of use.

Androgen deficiency: Cases of androgen deficiency have occurred with chronic use of opioids (see CLINICAL PHARMACOLOGY).

To report SUSPECTED ADVERSE REACTIONS, contact Amneal Pharmaceuticals at 1-877-835-5472 or FDA at 1-800-FDA-1088 or www.fda.gov/medwatch.

DRUG ABUSE AND DEPENDENCE

Controlled Substance

Tramadol HCl tablets contain tramadol, a Schedule IV controlled substance.

Abuse

Tramadol HCl contains tramadol, a substance with a high potential for abuse similar to other opioids. Tramadol HCl can be abused and is subject to misuse, addiction, and criminal diversion (see WARNINGS).

All patients treated with opioids require careful monitoring for signs of abuse and addiction, because use of opioid analgesic products carries the risk of addiction even under appropriate medical use.

Prescription drug abuse is the intentional non-therapeutic use of a prescription drug, even once, for its rewarding psychological or physiological effects.

Drug addiction is a cluster of behavioral, cognitive, and physiological phenomena that develop after repeated substance use and includes: a strong desire to take the drug, difficulties in controlling its use, persisting in its use despite harmful, or potentially harmful, consequences, a higher priority given to drug use than to other activities and obligations, increased tolerance, and sometimes a physical withdrawal.

“Drug-seeking” behavior is very common in persons with substance use disorders. Drug-seeking tactics include emergency calls or visits near the end of office hours, refusal to undergo appropriate examination, testing or referral, repeated “loss” of prescriptions, tampering with prescriptions and reluctance to provide prior medical records or contact information for other treating physician(s). “Doctor shopping” (visiting multiple prescribers to obtain additional prescriptions) is common among drug abusers and people suffering from untreated addiction. Preoccupation with achieving adequate pain relief can be appropriate behavior in a patient with poor pain control.

Abuse and addiction are separate and distinct from physical dependence and tolerance. Healthcare providers should be aware that addiction may not be accompanied by concurrent tolerance and symptoms of physical dependence in all addicts. In addition, abuse of opioids can occur in the absence of true addiction.

Tramadol HCl, like other opioids, can be diverted for non-medical use into illicit channels of distribution. Careful record-keeping of prescribing information, including quantity, frequency, and renewal requests, as required by state and federal law, is strongly advised.

Proper assessment of the patient, proper prescribing practices, periodic re-evaluation of therapy, and proper dispensing and storage are appropriate measures that help to limit abuse of opioid drugs.

Risks Specific to Abuse of Tramadol HCl

Tramadol HCl is intended for oral use only. Abuse of tramadol HCl poses a risk of overdose and death. The risk is increased with concurrent abuse of tramadol HCl with alcohol and other central nervous system depressants.

Parenteral drug abuse is commonly associated with transmission of infectious diseases such as hepatitis and HIV.

Dependence

Both tolerance and physical dependence can develop during chronic opioid therapy. Tolerance is the need for increasing doses of drugs to maintain a defined effect such as analgesia (in the absence of disease progression or other external factors). Tolerance may occur to both the desired and undesired effects of drugs, and may develop at different rates for different effects.

Physical dependence results in withdrawal symptoms after abrupt discontinuation or a significant dosage reduction of a drug. Withdrawal also may be precipitated through the administration of drugs with opioid antagonist activity (e.g., naloxone, nalmefene), mixed agonist/antagonist analgesics (pentazocine, butorphanol, nalbuphine), or partial agonists (buprenorphine). Physical dependence may not occur to a clinically significant degree until after several days to weeks of continued opioid usage.

Tramadol HCl should not be abruptly discontinued in a physically dependent patient (see DOSAGE AND ADMINISTRATION). If tramadol HCl is abruptly discontinued in a physically-dependent patient, a withdrawal syndrome may occur. Some or all of the following can characterize this syndrome: restlessness, lacrimation, rhinorrhea, yawning, perspiration, chills, myalgia, and mydriasis. Other signs and symptoms also may develop, including: irritability, anxiety, backache, joint pain, weakness, abdominal cramps, insomnia, nausea, anorexia, vomiting, diarrhea, or increased blood pressure, respiratory rate, or heart rate.

Infants born to mothers physically dependent on opioids will also be physically dependent and may exhibit respiratory difficulties and withdrawal signs (see PRECAUTIONS; Pregnancy).

OVERDOSAGE

Clinical Presentation

Acute overdosage with tramadol HCl can be manifested by respiratory depression, somnolence progressing to stupor or coma, skeletal muscle flaccidity, cold and clammy skin, constricted pupils, and, in some cases, pulmonary edema, bradycardia, hypotension, partial or complete airway obstruction, atypical snoring, seizures, and death. Marked mydriasis rather than miosis may be seen with hypoxia in overdose situations.

Deaths due to overdose have been reported with abuse and misuse of tramadol (see WARNINGS; Addiction, Abuse, and Misuse). Review of case reports has indicated that the risk of fatal overdose is further increased when tramadol is abused concurrently with alcohol or other CNS depressants, including other opioids.

Treatment of Overdose

In case of overdose, priorities are the re-establishment of a patent and protected airway and institution of assisted or controlled ventilation, if needed. Employ other supportive measures (including oxygen and vasopressors) in the management of circulatory shock and pulmonary edema as indicated. Cardiac arrest or serious arrhythmias will require advanced life-supporting measures.

The opioid antagonists, naloxone or nalmefene, are specific antidotes to respiratory depression resulting from opioid overdose. For clinically significant respiratory or circulatory depression secondary to tramadol overdose, administer an opioid antagonist. Opioid antagonists should not be administered in the absence of clinically significant respiratory or circulatory depression secondary to tramadol overdose.

While naloxone will reverse some, but not all, symptoms caused by overdosage with tramadol, the risk of seizures is also increased with naloxone administration. In animals, convulsions following the administration of toxic doses of tramadol HCl could be suppressed with barbiturates or benzodiazepines but were increased with naloxone. Naloxone administration did not change the lethality of an overdose in mice. Hemodialysis is not expected to be helpful in an overdose because it removes less than 7% of the administered dose in a 4-hour dialysis period.

Because the duration of opioid reversal is expected to be less than the duration of action of tramadol in tramadol HCl, carefully monitor the patient until spontaneous respiration is reliably re-established. If the response to an opioid antagonist is suboptimal or only brief in nature, administer additional antagonist as directed by the product’s prescribing information.

In an individual physically dependent on opioids, administration of the recommended usual dosage of the antagonist will precipitate an acute withdrawal syndrome. The severity of the withdrawal symptoms experienced will depend on the degree of physical dependence and the dose of the antagonist administered. If a decision is made to treat serious respiratory depression in the physically dependent patient, administration of the antagonist should be begun with care and by titration with smaller than usual doses of the antagonist.

DOSAGE AND ADMINISTRATION

Adults (17 years of age and over)

Important Dosage and Administration Instructions

Use the lowest effective dosage for the shortest duration consistent with individual patient treatment goals (see WARNINGS).

Initiate the dosing regimen for each patient individually, taking into account the patient's severity of pain, patient response, prior analgesic treatment experience, and risk factors for addiction, abuse, and misuse (see WARNINGS).

Monitor patients closely for respiratory depression, especially within the first 24 to 72 hours of initiating therapy and following dosage increases with tramadol HCl tablets and adjust the dosage accordingly (see WARNINGS).

Initial Dosage

Initiating Treatment with Tramadol HCl tablets

For patients with moderate to moderately severe chronic pain not requiring rapid onset of analgesic effect, the tolerability of tramadol HCl tablets can be improved by initiating therapy with the following titration regimen: tramadol HCl tablets should be started at 25 mg/day qAM and titrated in 25 mg increments as separate doses every 3 days to reach 100 mg/day (25 mg four times a day). Thereafter the total daily dose may be increased by 50 mg as tolerated every 3 days to reach 200 mg/day (50 mg four times a day). After titration, tramadol HCl tablets 50 to 100 mg can be administered as needed for pain relief every 4 to 6 hours not to exceed 400 mg/day.

For the subset of patients for whom rapid onset of analgesic effect is required and for whom the benefits outweigh the risk of discontinuation due to adverse events associated with higher initial doses, tramadol HCl tablets 50 mg to 100 mg can be administered as needed for pain relief every four to six hours, not to exceed 400 mg per day.

Conversion from Tramadol HCl tablets to Extended-Release tramadol

The relative bioavailability of tramadol HCl tablets compared to extended-release tramadol is unknown, so conversion to extended-release formulations must be accompanied by close observation for signs of excessive sedation and respiratory depression.

Dosage Modification in Patients with Hepatic Impairment

The recommended dose for adult patients with cirrhosis is 50 mg every 12 hours.

Dosage Modification in Patients with Renal Impairment

In all patients with creatinine clearance less than 30 mL/min, it is recommended that the dosing interval of tramadol HCl tablets be increased to 12 hours, with a maximum daily dose of 200 mg. Since only 7% of an administered dose is removed by hemodialysis, dialysis patients can receive their regular dose on the day of dialysis.

Dosage Modification in Geriatric Patients

In general, dose selection for an elderly patient over 65 years old should be cautious, usually starting at the low end of the dosing range, reflecting the greater frequency of decreased hepatic, renal or cardiac function and of concomitant disease or other drug therapy. For elderly patients over 75 years old, total dose should not exceed 300 mg/day.

Titration and Maintenance of Therapy

Individually titrate tramadol HCl tablets to a dose that provides adequate analgesia and minimizes adverse reactions. Continually reevaluate patients receiving tramadol HCl tablets to assess the maintenance of pain control and the relative incidence of adverse reactions, as well as monitoring for the development of addiction, abuse, or misuse (see WARNINGS). Frequent communication is important among the prescriber, other members of the healthcare team, the patient, and the caregiver/family during periods of changing analgesic requirements, including initial titration.

If the level of pain increases after dosage stabilization, attempt to identify the source of increased pain before increasing the tramadol HCl tablet dosage. If unacceptable opioid-related adverse reactions are observed, consider reducing the dosage. Adjust the dosage to obtain an appropriate balance between management of pain and opioid-related adverse reactions.

Discontinuation of Tramadol HCl Tablets

When a patient who has been taking tramadol HCl tablets regularly and may be physically dependent no longer requires therapy with tramadol HCl tablets, taper the dose gradually, by 25% to 50% every 2 to 4 days, while monitoring carefully for signs and symptoms of withdrawal. If the patient develops these signs or symptoms, raise the dose to the previous level and taper more slowly, either by increasing the interval between decreases, decreasing the amount of change in dose, or both. Do not abruptly discontinue tramadol HCl tablets in a physically-dependent patient (see WARNINGS; Drug Abuse and Dependence).

HOW SUPPLIED

Tramadol HCl tablets, USP, 50 mg, are supplied as unscored, white, round film-coated tablets debossed AN over 627.

They are supplied as follows:

NDC 68071-4119-5 Bottles of 15

NDC 68071-4119-3 Bottles of 30

NDC 68071-4119-4 Bottles of 40

NDC 68071-4119-6 Bottles of 60

NDC 68071-4119-7 Bottles of 84

NDC 68071-4119-9 Bottles of 90

NDC 68071-4119-1 Bottles of 120

NDC 68071-4119- 8 Bottles of 180

Store at 20° to 25°C (68° to 77°F); excursions permitted between 15° to30°C (59° to 86°F) [see USP Controlled Room Temperature]. Dispense in a tight container as defined in the USP.

Manufactured by:
Amneal Pharmaceuticals of NY LLC
Brookhaven, NY 11719

Distributed by:
Amneal Pharmaceuticals LLC
Glasgow, KY 42141

Rev. 03-2017-04

Medication Guide

Tramadol (TRAM-a-dol) Hydrochloride Tablets, USP, CIV

Tramadol HCl tablets are:

- A strong prescription pain medicine that contains an opioid (narcotic) that is used for the management pain in adults, when other pain treatments such as non-opioid pain medicines do not treat your pain well enough or you cannot tolerate them.
- An opioid pain medicine that can put you at risk for overdose and death. Even if you take your dose correctly as prescribed you are at risk for opioid addiction, abuse, and misuse that can lead to death.

Important information about tramadol HCl tablets:

- Get emergency help right away if you take too much tramadol HCl tablets (overdose). When you first start taking tramadol HCl tablets, when your dose is changed, or if you take too much (overdose), serious or life-threatening breathing problems that can lead to death may occur.
- Taking tramadol HCl tablets with other opioid medicines, benzodiazepines, alcohol, or other central nervous system depressants (including street drugs) can cause severe drowsiness, decreased awareness, breathing problems, coma, and death.
- Never give anyone else your tramadol HCl tablets. They could die from taking it. Store tramadol HCl tablets away from children and in a safe place to prevent stealing or abuse. Selling or giving away tramadol HCl tablets is against the law.

Do not take tramadol HCl tablets if you have:

- Severe asthma, trouble breathing, or other lung problems.
- A bowel blockage or have narrowing of the stomach or intestines.
- An allergy to tramadol.
- Taken a Monoamine Oxidase Inhibitor, MAOI, (medicine used for depression) within the last 14 days.

Before taking tramadol HCl tablets, tell your healthcare provider if you have a history of:

- head injury, seizures
- problems urinating
- abuse of street or prescription drugs, alcohol addiction, or mental health problems.
- liver, kidney, thyroid problems
- pancreas or gallbladder problems

Tell your healthcare provider if you are:

- pregnant or planning to become pregnant. Prolonged use of tramadol HCl tablets during pregnancy can cause withdrawal symptoms in your newborn baby that could be life-threatening if not recognized and treated.
- breastfeeding. Tramadol HCl passes into breast milk and may harm your baby.
- taking prescription or over-the-counter medicines, vitamins, or herbal supplements. Taking tramadol HCl tablets with certain other medicines can cause serious side effects that could lead to death.

When taking tramadol HCl tablets:

- Do not change your dose. Take tramadol HCl tablets exactly as prescribed by your healthcare provider. Use the lowest dose possible for the shortest time needed.
- Take your prescribed dose as indicated by your health care provider. The maximum dosage is 1 or 2 tablets every 4 to 6 hours, as needed for pain relief. Do not take more than your prescribed dose and do not take more than 8 tablets per day. If you miss a dose, take your next dose at your usual time.
- Call your healthcare provider if the dose you are taking does not control your pain.
- If you have been taking tramadol HCl tablets regularly, do not stop taking tramadol HCl tablets without talking to your healthcare provider.
- After you stop taking tramadol HCl tablets, ask your pharmacist how to dispose of any unused tablets.

While taking tramadol HCl tablets DO NOT:

- Drive or operate heavy machinery, until you know how tramadol HCl affects you. Tramadol HCl tablets can make you sleepy, dizzy, or lightheaded.
- Drink alcohol or use prescription or over-the-counter medicines that contain alcohol. Using products containing alcohol during treatment with tramadol HCl tablets may cause you to overdose and die.

The possible side effects of tramadol HCl tablets:

- constipation, nausea, sleepiness, vomiting, tiredness, headache, dizziness, abdominal pain. Call your healthcare provider if you have any of these symptoms and they are severe.
  Get emergency medical help if you have:
- trouble breathing, shortness of breath, fast heartbeat, chest pain, swelling of your face, tongue, or throat, extreme drowsiness, light-headedness when changing positions, feeling faint, agitation, high body temperature, trouble walking, stiff muscles, or mental changes such as confusion.

These are not all the possible side effects of tramadol HCl tablets. Call your doctor for medical advice about side effects. You may report side effects to FDA at 1-800-FDA-1088. For more information go to dailymed.nlm.nih.gov

Manufactured by:
Amneal Pharmaceuticals of NY LLC
Brookhaven, NY 11719

Distributed by:
Amneal Pharmaceuticals LLC
Glasgow, KY 42141

Rev. 03-2017-00

This Medication Guide has been approved by the U.S. Food and Drug Administration.